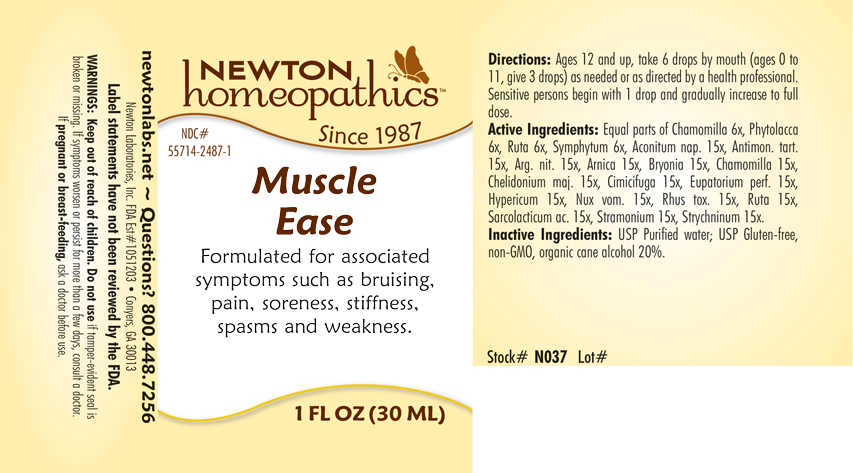 DRUG LABEL: Muscle Ease
NDC: 55714-2487 | Form: LIQUID
Manufacturer: Newton Laboratories, Inc.
Category: homeopathic | Type: HUMAN OTC DRUG LABEL
Date: 20250207

ACTIVE INGREDIENTS: COMFREY ROOT 6 [hp_X]/1 mL; ACONITUM NAPELLUS 15 [hp_X]/1 mL; ANTIMONY POTASSIUM TARTRATE 15 [hp_X]/1 mL; SILVER NITRITE 15 [hp_X]/1 mL; ARNICA MONTANA 15 [hp_X]/1 mL; BRYONIA ALBA ROOT 15 [hp_X]/1 mL; CHELIDONIUM MAJUS 15 [hp_X]/1 mL; BLACK COHOSH 15 [hp_X]/1 mL; EUPATORIUM PERFOLIATUM FLOWERING TOP 15 [hp_X]/1 mL; MATRICARIA CHAMOMILLA 15 [hp_X]/1 mL; STRYCHNOS NUX-VOMICA SEED 15 [hp_X]/1 mL; TOXICODENDRON PUBESCENS LEAF 15 [hp_X]/1 mL; RUTA GRAVEOLENS FLOWERING TOP 15 [hp_X]/1 mL; LACTIC ACID, L- 15 [hp_X]/1 mL; DATURA STRAMONIUM 15 [hp_X]/1 mL; STRYCHNINE 15 [hp_X]/1 mL; PHYTOLACCA AMERICANA ROOT 6 [hp_X]/1 mL; HYPERICUM PERFORATUM 15 [hp_X]/1 mL
INACTIVE INGREDIENTS: WATER; ALCOHOL

Muscle 2487L

INDICATIONS & USAGE SECTION

Formulated for associated symptoms such as bruising, pain, soreness, stiffness, spasms and weakness..

DOSAGE & ADMINISTRATION SECTION

Directions: Ages 12 and up, take 6 drops by mouth (ages 0 to 11, give 3 drops) as needed or as directed by a health professional. Sensitive persons begin with 1 drop and gradually increase to full dose.

OTC - ACTIVE INGREDIENT SECTION

Equal parts of Chamomilla 6x, Phytolacca decandra 6x, Ruta graveolens 6x, Symphytum officinale 6x, Aconitum napellus 15x, Antimonium tartaricum 15x, Argentum nitricum 15x, Arnica montana 15x, Bryonia 15x, Chamomilla 15x, Chelidonium majus 15x, Cimicifuga racemosa 15x, Eupatorium perfoliatum 15x, Hypericum perforatum 15x, Nux vomica 15x, Rhus toxicodendron 15x, Ruta graveolens 15x, Sarcolacticum acidum 15x, Stramonium 15x, Strychninum 15

OTC - PURPOSE SECTION

Formulated for associated symptoms such as bruising, pain, soreness, stiffness, spasms and weakness.

INACTIVE INGREDIENT SECTION

Inactive Ingredients: USP Purified Water; USP Gluten-free, non-GMO, organic cane alcohol 20%.

QUESTIONS SECTION

newtonlabs.net – Questions? 800.448.7256

Newton Laboratories, Inc. FDA Est # 1051203 - Conyers, GA 30013

WARNINGS SECTION

WARNINGS: Keep out of reach of children. Do not use if tamper-evident seal is broken or missing. If symptoms worsen or persist for more than a few days, consult a doctor. If pregnant or breast-feeding, ask a doctor before use.

OTC - PREGNANCY OR BREAST FEEDING SECTION

If pregnant or breast-feeding, ask a doctor before use.

OTC - KEEP OUT OF REACH OF CHILDREN SECTION

Keep out of reach of children.